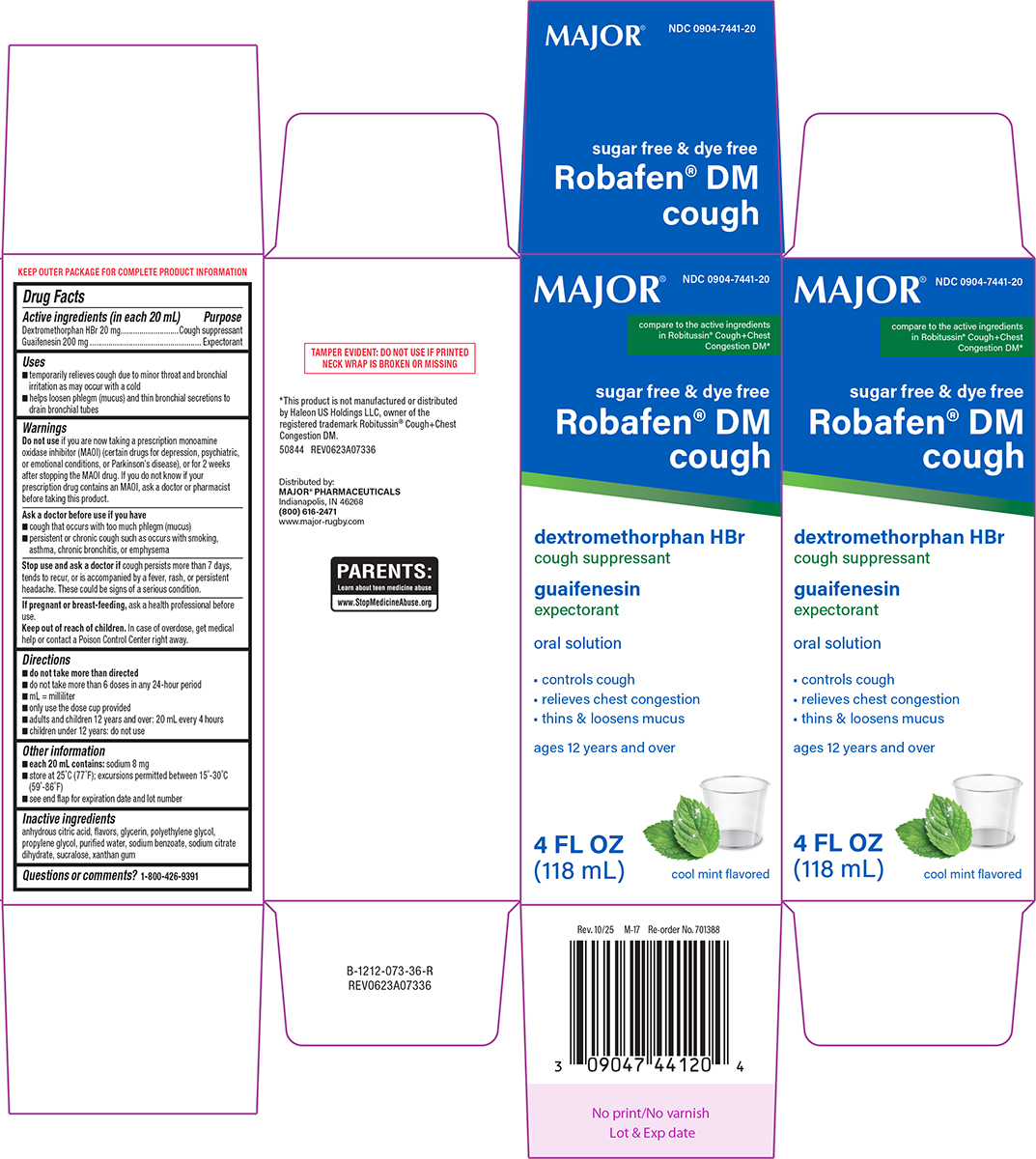 DRUG LABEL: Robafen DM Cough
NDC: 0904-7441 | Form: SOLUTION
Manufacturer: Major Pharmaceuticals
Category: otc | Type: HUMAN OTC DRUG LABEL
Date: 20260203

ACTIVE INGREDIENTS: DEXTROMETHORPHAN HYDROBROMIDE 20 mg/20 mL; GUAIFENESIN 200 mg/20 mL
INACTIVE INGREDIENTS: ANHYDROUS CITRIC ACID; GLYCERIN; POLYETHYLENE GLYCOL, UNSPECIFIED; PROPYLENE GLYCOL; WATER; SODIUM BENZOATE; TRISODIUM CITRATE DIHYDRATE; SUCRALOSE; XANTHAN GUM

Major 44-073

Active ingredients (in each 20 mL)

Dextromethorphan HBr 20 mg
Guaifenesin 200 mg

Purpose

Cough suppressant
Expectorant

Uses

- temporarily relieves cough due to minor throat and bronchial irritation as may occur with a cold
- helps loosen phlegm (mucus) and thin bronchial secretions to drain bronchial tubes

Warnings

Do not use

if you are now taking a prescription monoamine oxidase inhibitor (MAOI) (certain drugs for depression, psychiatric, or emotional conditions, or Parkinson’s disease), or for 2 weeks after stopping the MAOI drug. If you do not know if your prescription drug contains an MAOI, ask a doctor or pharmacist before taking this product.

Ask a doctor before use if you have

- cough that occurs with too much phlegm (mucus)
- persistent or chronic cough such as occurs with smoking, asthma, chronic bronchitis, or emphysema

Stop use and ask a doctor if

cough persists more than 7 days, tends to recur, or is accompanied by a fever, rash, or persistent headache. These could be signs of a serious condition.

If pregnant or breast-feeding,

ask a health professional before use.

Keep out of reach of children.

In case of overdose, get medical help or contact a Poison Control Center right away.

Directions

- do not take more than directed
- do not take more than 6 doses in any 24-hour period
- mL = milliliter
- only use the dose cup provided
- adults and children 12 years and over: 20 mL every 4 hours
- children under 12 years: do not use

Other information

- each 20 mL contains: sodium 8 mg
- store at 25°C (77°F); excursions permitted between 15°-30°C (59°-86°F)
- see end flap for expiration date and lot number

Inactive ingredients

anhydrous citric acid, flavors, glycerin, polyethylene glycol, propylene glycol, purified water, sodium benzoate, sodium citrate dihydrate, sucralose, xanthan gum

Questions or comments?

1-800-426-9391

Principal display panel

MAJOR®

NDC 0904-7441-20
Compare to the active
ingredients in Robitussin®
Cough+Chest Congestion DM*

Sugar Free & Dye Free
Robafen® DM
Cough
Dextromethorphan HBr
cough suppressant
Guaifenesin
expectorant

Oral Solution

• Controls Cough
• Relieves Chest Congestion
• Thins & Loosens Mucus

Ages 12 Years and Over

Cool Mint Flavored

4 FL OZ (118 mL)

TAMPER EVIDENT: DO NOT USE IF PRINTED
NECK WRAP IS BROKEN OR MISSING

*This product is not manufactured or distributed
by Haleon US Holdings LLC, owner of the
registered trademark Robitussin® Cough+Chest
Congestion DM.
50844 REV0623A07336

Distributed by:
MAJOR® PHARMACEUTICALS
Indianapolis, IN 46268
(800) 616-2471
www.major-rugby.com

Major 44-073